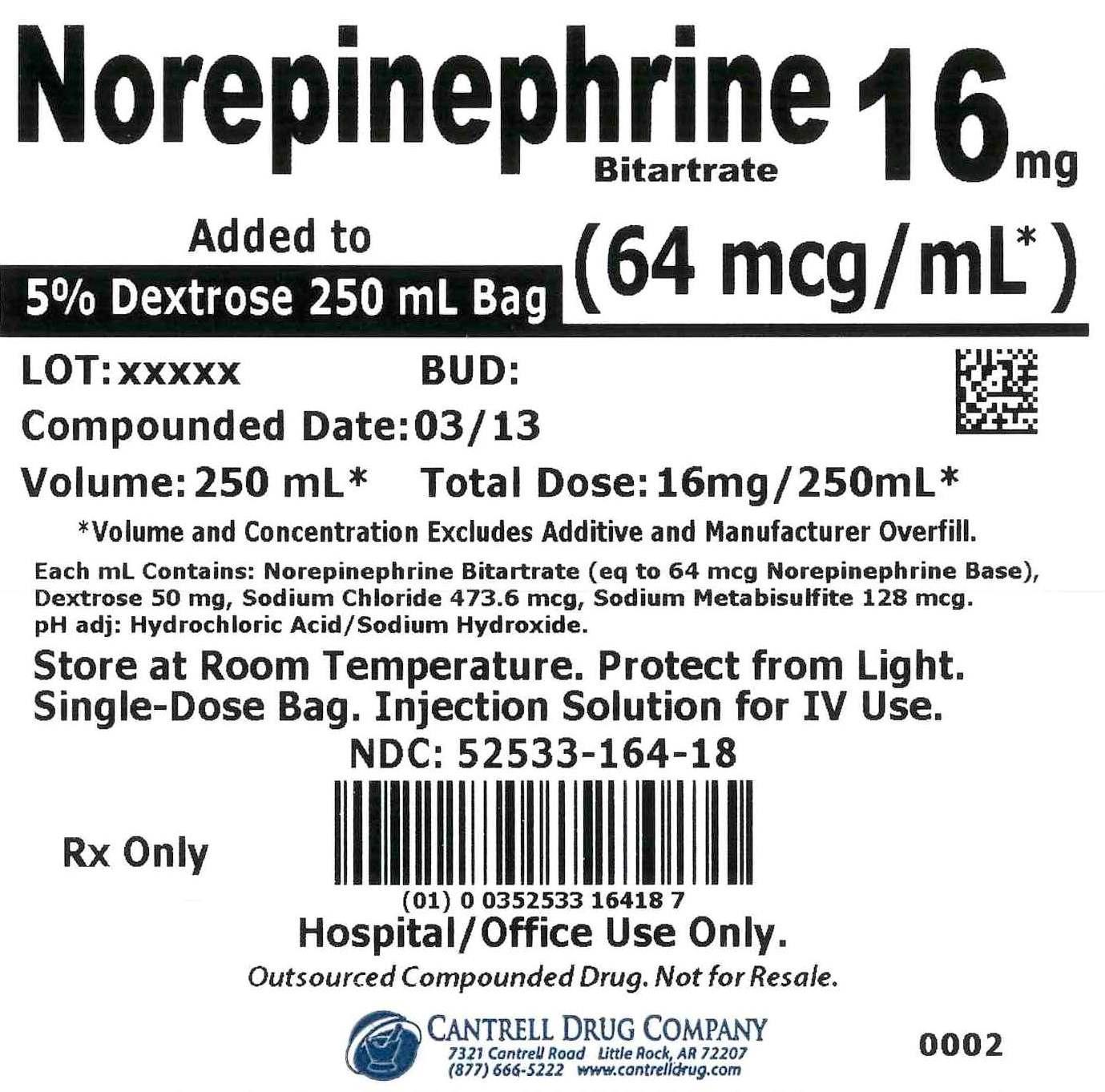 DRUG LABEL: Norepinephrine Bitartrate
NDC: 52533-164 | Form: INJECTION, SOLUTION
Manufacturer: Cantrell Drug Company
Category: prescription | Type: HUMAN PRESCRIPTION DRUG LABEL
Date: 20150312

ACTIVE INGREDIENTS: Norepinephrine Bitartrate 64 ug/1 mL
INACTIVE INGREDIENTS: ANHYDROUS DEXTROSE 50 mg/1 mL; SODIUM CHLORIDE 473.6 ug/1 mL; SODIUM METABISULFITE 128 ug/1 mL; WATER

Norepinephrine Bitartrate 16 mg Added to 5% Dextrose 250 mL Bag

• WARNINGS AND PRECAUTIONS

Outsourced Compounded Drug. Not for Resale. Hospital/Office Use Only.

• ADVERSE EVENTS

To facilitate Adverse Event Reporting: www.fda.gov/medwatch or 1-800-FDA-1088.

• HOW SUPPLIED

Norepinephrine bitartrate injection solution is supplied as a sterile, nonpyrogenic solution that is clear, colorless at 250 mL in a Single-Dose Injection Solution Bag.

This product is Preservative-Free and Latex-Free.

• INGREDIENTS

Each 1 mL contains the equivalent of 64 mcg norepinephrine base, 50 mg dextrose, 473.6 mcg sodium chloride, 128 mcg sodium metabisulfite, and pH adjusters include hydrochloric acid and/or sodium hydroxide, if necessary.

• STORAGE AND HANDLING

Store at 20° to 25°C (68° to 77°F). [See USP Controlled Room Temperature]. Protect from light.

Parenteral drug products should be inspected visually for particulate matter and discoloration prior to use, whenever solution and container permit.

Do not use the solution if its color is pinkish or darker than slightly yellow or if it contains a precipitate.

• DOSAGE AND ADMINISTRATION.

FOR INTRAVENOUS USE ONLY. PRESERVATIVE-FREE INJECTION SOLUTION.

Rx Only

Rev. 03/15

CANTRELL DRUG COMPANY
LITTLE ROCK, AR 72207